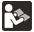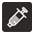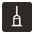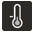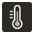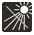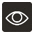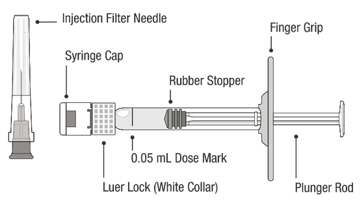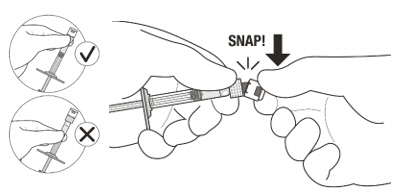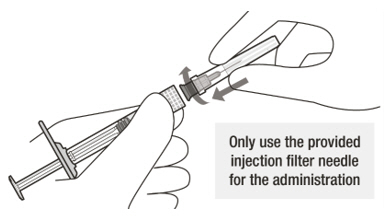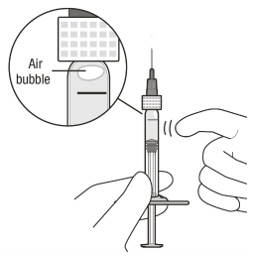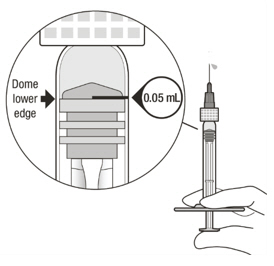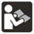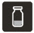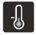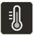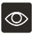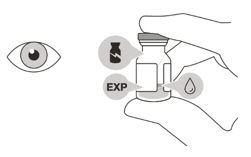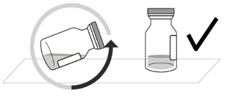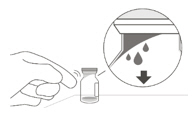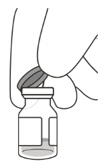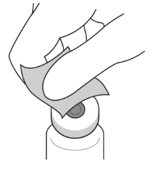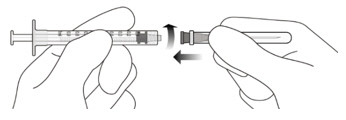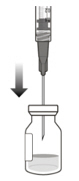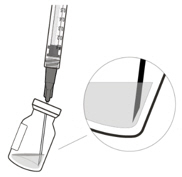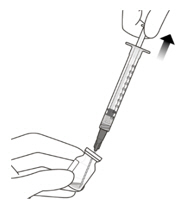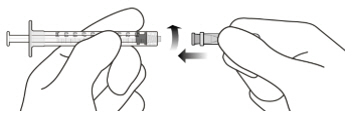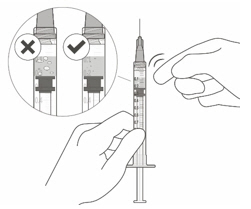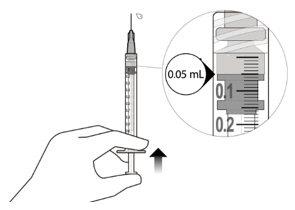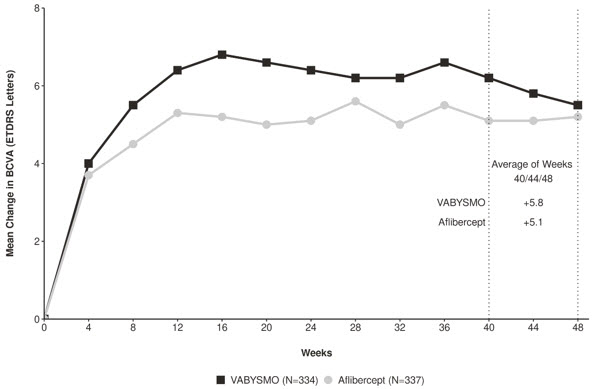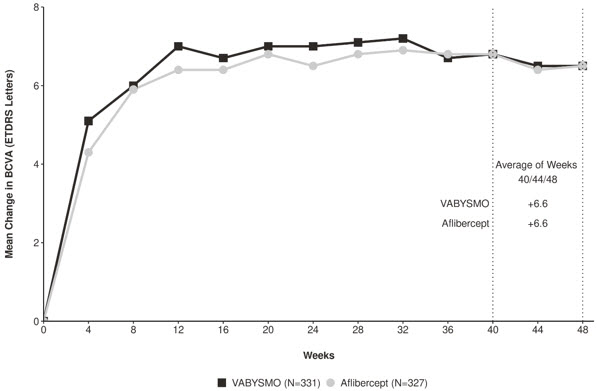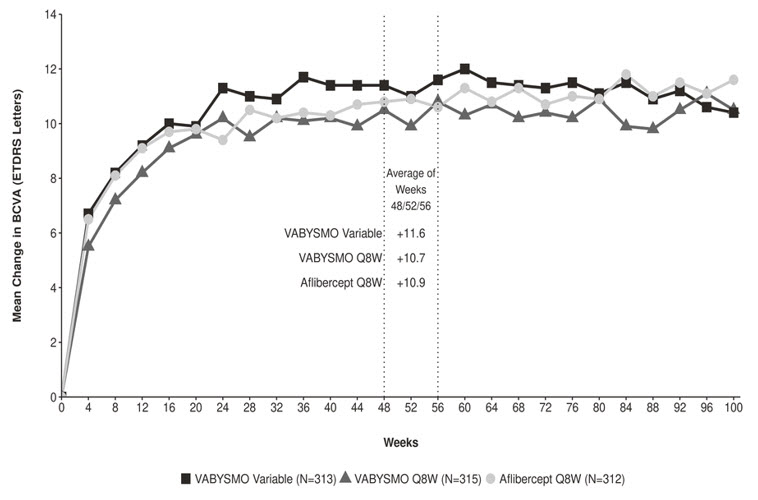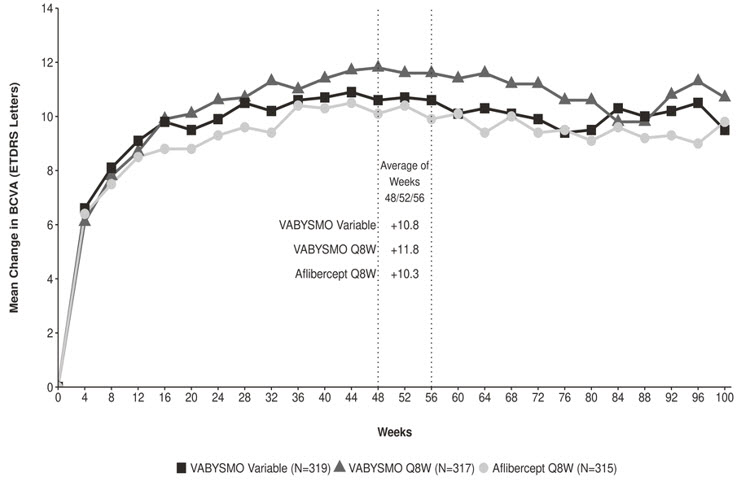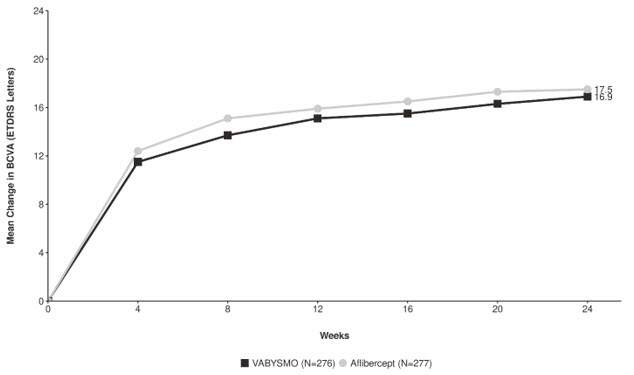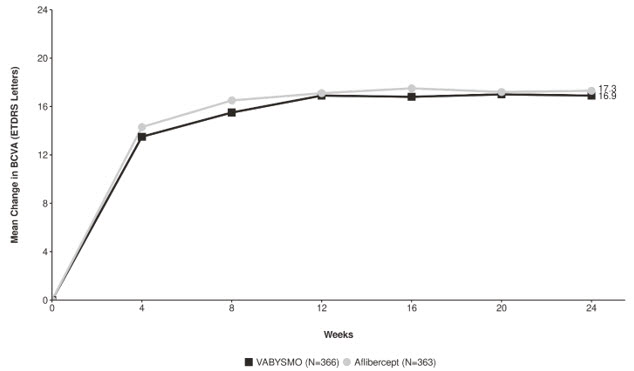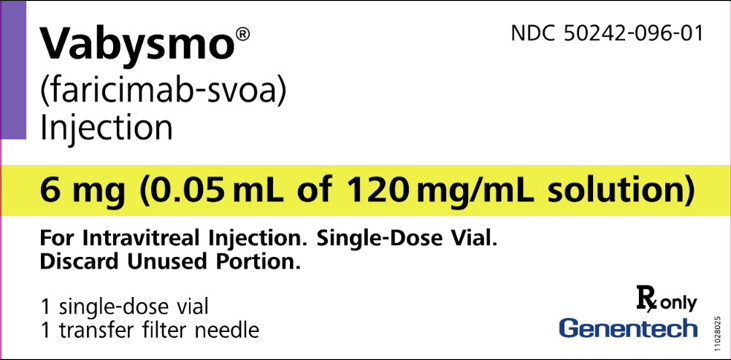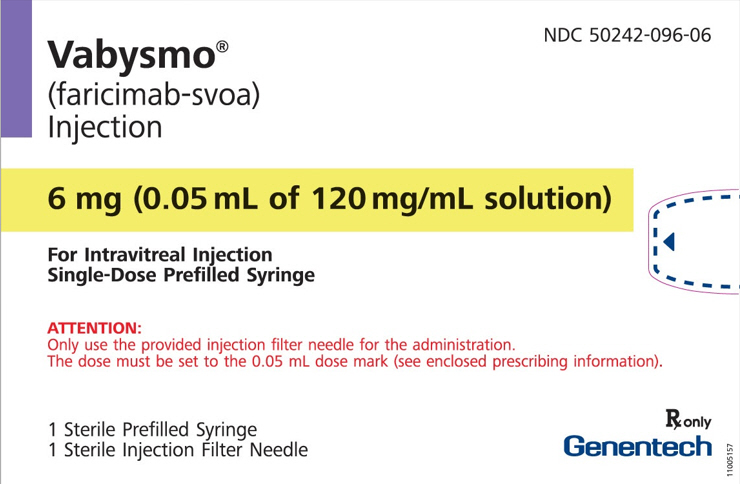 DRUG LABEL: VABYSMO
NDC: 50242-096 | Form: INJECTION, SOLUTION
Manufacturer: Genentech, Inc.
Category: prescription | Type: HUMAN PRESCRIPTION DRUG LABEL
Date: 20260120

ACTIVE INGREDIENTS: FARICIMAB 6 mg/0.05 mL
INACTIVE INGREDIENTS: HISTIDINE 155 ug/0.05 mL; METHIONINE 52.2 ug/0.05 mL; SODIUM CHLORIDE 73.1 ug/0.05 mL; SUCROSE 2.74 mg/0.05 mL; POLYSORBATE 20 20 ug/0.05 mL; WATER; ACETIC ACID

HIGHLIGHTS OF PRESCRIBING INFORMATION

These highlights do not include all the information needed to use VABYSMO safely and effectively. See full prescribing information for VABYSMO.
VABYSMO® (faricimab-svoa) injection, for intravitreal use
Initial U.S. Approval: 2022

RECENT MAJOR CHANGES

Indications and Usage, Macular Edema Following Retinal Vein Occlusion (RVO) (1.3) | 10/2023
Dosage and Administration, General Dosing Information (2.1) | 7/2024
Dosage and Administration, Macular Edema Following Retinal Vein Occlusion (2.4) | 10/2023
Dosage and Administration, Preparation for Administration - Prefilled Syringe (2.5) | 7/2024
Dosage and Administration, Injection Procedure (2.7) | 7/2024
Warnings and Precautions, Retinal Vasculitis and/or Retinal Vascular Occlusion (5.4) | 10/2023

1 INDICATIONS AND USAGE

VABYSMO is a vascular endothelial growth factor (VEGF) and angiopoietin-2 (Ang-2) inhibitor indicated for the treatment of patients with:

- Neovascular (Wet) Age-Related Macular Degeneration (nAMD) (1.1)
- Diabetic Macular Edema (DME) (1.2)
- Macular Edema Following Retinal Vein Occlusion (RVO) (1.3)

2 DOSAGE AND ADMINISTRATION

For intravitreal injection. (2.1)

- Neovascular (Wet) Age-Related Macular Degeneration (nAMD)
  - The recommended dose for VABYSMO is 6 mg (0.05 mL of 120 mg/mL solution) administered by intravitreal injection every 4 weeks (approximately every 28 ± 7 days, monthly) for the first 4 doses, followed by optical coherence tomography and visual acuity evaluations 8 and 12 weeks later to inform whether to give a 6 mg dose via intravitreal injection on one of the following three regimens: 1) Weeks 28 and 44; 2) Weeks 24, 36 and 48; or 3) Weeks 20, 28, 36 and 44. Although additional efficacy was not demonstrated in most patients when VABYSMO was dosed every 4 weeks compared to every 8 weeks, some patients may need every 4 week (monthly) dosing after the first 4 doses. Patients should be assessed regularly. (2.2)
- Diabetic Macular Edema (DME)
  - VABYSMO is recommended to be dosed by following one of these two dose regimens: 1) 6 mg (0.05 mL of 120 mg/mL solution) administered by intravitreal injection every 4 weeks (approximately every 28 days ± 7 days, monthly) for at least 4 doses. If after at least 4 doses, resolution of edema based on the central subfield thickness (CST) of the macula as measured by optical coherence tomography is achieved, then the interval of dosing may be modified by extensions of up to 4 week interval increments or reductions of up to 8 week interval increments based on CST and visual acuity evaluations; or 2) 6 mg dose of VABYSMO can be administered every 4 weeks for the first 6 doses, followed by 6 mg dose via intravitreal injection at intervals of every 8 weeks (2 months). Although additional efficacy was not demonstrated in most patients when VABYSMO was dosed every 4 weeks compared to every 8 weeks, some patients may need every 4 week (monthly) dosing after the first 4 doses. Patients should be assessed regularly. (2.3)
- Macular Edema Following Retinal Vein Occlusion (RVO)
  - The recommended dose for VABYSMO is 6 mg (0.05 mL of 120 mg/mL) administered by intravitreal injection every 4 weeks (approximately every 28 ± 7 days, monthly) for 6 months. (2.4)

3 DOSAGE FORMS AND STRENGTHS

- Injection: 6 mg (0.05 mL of 120 mg/mL solution) in a single-dose prefilled syringe (3)
- Injection: 6 mg (0.05 mL of 120 mg/mL solution) in a single-dose vial (3)

4 CONTRAINDICATIONS

- Ocular or periocular infection (4.1)
- Active intraocular inflammation (4.2)
- Hypersensitivity (4.3)

5 WARNINGS AND PRECAUTIONS

- Endophthalmitis and retinal detachments may occur following intravitreal injections. Patients should be instructed to report any symptoms suggestive of endophthalmitis or retinal detachment without delay, to permit prompt and appropriate management. (5.1)
- Increases in intraocular pressure have been seen within 60 minutes of an intravitreal injection. (5.2)
- There is a potential risk of arterial thromboembolic events (ATEs) associated with VEGF inhibition. (5.3)

6 ADVERSE REACTIONS

The most common adverse reactions (≥ 5%) reported in patients receiving VABYSMO were cataract (15%) and conjunctival hemorrhage (8%). (6.1)

To report SUSPECTED ADVERSE REACTIONS, contact Genentech at 1-888-835-2555 or FDA at 1-800-FDA-1088 or www.fda.gov/medwatch.

FULL PRESCRIBING INFORMATION

1 INDICATIONS AND USAGE

VABYSMO is a vascular endothelial growth factor (VEGF) and angiopoietin 2 (Ang-2) inhibitor indicated for the treatment of patients with:

2 DOSAGE AND ADMINISTRATION

2.1 General Dosing Information

For intravitreal injection. VABYSMO must be administered by a qualified physician.

VABYSMO is available as:

- Prefilled syringe: A sterile injection filter needle (30-gauge × ½-inch, Extra Thin Wall) with an integrated filter in the hub is provided. Each prefilled syringe should only be used for the treatment of a single eye.
- Vial: A sterile 5-micron, blunt transfer filter needle (18-gauge × 1½-inch) is provided. Each vial should only be used for the treatment of a single eye.

[see How Supplied/Storage and Handling (16)]

2.2 Neovascular (wet) Age-Related Macular Degeneration (nAMD)

The recommended dose for VABYSMO is 6 mg (0.05 mL of 120 mg/mL solution) administered by intravitreal injection every 4 weeks (approximately every 28 ± 7 days, monthly) for the first 4 doses, followed by optical coherence tomography and visual acuity evaluations 8 and 12 weeks later to inform whether to give a 6 mg dose via intravitreal injection on one of the following three regimens: 1) Weeks 28 and 44; 2) Weeks 24, 36 and 48; or 3) Weeks 20, 28, 36 and 44. Although additional efficacy was not demonstrated in most patients when VABYSMO was dosed every 4 weeks compared to every 8 weeks, some patients may need every 4 week (monthly) dosing after the first 4 doses. Patients should be assessed regularly.

2.3 Diabetic Macular Edema (DME)

VABYSMO is recommended to be dosed by following one of these two dose regimens: 1) 6 mg (0.05 mL of 120 mg/mL solution) administered by intravitreal injection every 4 weeks (approximately every 28 days ± 7 days, monthly) for at least 4 doses. If after at least 4 doses, resolution of edema based on the central subfield thickness (CST) of the macula as measured by optical coherence tomography is achieved, then the interval of dosing may be modified by extensions of up to 4 week interval increments or reductions of up to 8 week interval increments based on CST and visual acuity evaluations; or 2) 6 mg dose of VABYSMO can be administered every 4 weeks for the first 6 doses, followed by 6 mg dose via intravitreal injection at intervals of every 8 weeks (2 months). Although additional efficacy was not demonstrated in most patients when VABYSMO was dosed every 4 weeks compared to every 8 weeks, some patients may need every 4 week (monthly) dosing after the first 4 doses. Patients should be assessed regularly.

2.4 Macular Edema Following Retinal Vein Occlusion (RVO)

The recommended dose for VABYSMO is 6 mg (0.05 mL of 120 mg/mL solution) administered by intravitreal injection every 4 weeks (approximately every 28 ± 7 days, monthly) for 6 months.

2.5 Preparation for Administration - Prefilled Syringe

Before you start

Read all the instructions carefully before using VABYSMO.

The VABYSMO carton includes:

A sterile prefilled syringe in a sealed tray. The prefilled syringe is for treatment of a single eye.

A sterile injection filter needle (30-gauge × ½ inch, Extra Thin Wall) with an integrated filter in the hub. The injection filter needle is for single use only.

Only use the provided injection filter needle for the administration.

VABYSMO should be refrigerated at temperatures between 2°C to 8°C (36°F to 46°F).
Do not freeze.

Allow VABYSMO to reach room temperature, 20°C to 25°C (68°F to 77°F) before proceeding with the administration.

Prior to use, keep the sealed tray in the original carton to protect the prefilled syringe from light. The prefilled syringe may be kept at room temperature in the original carton for up to 24 hours.

VABYSMO should be inspected visually prior to administration.

Do not use if the carton seals have been tampered with.

Do not use if the packaging, prefilled syringe, injection filter needle is expired, damaged, or have been tampered with.

Do not use if the injection filter needle is missing.

Do not remove the finger grip from the syringe.

Do not use if the syringe cap is detached from the Luer lock.

Do not use if particulates, cloudiness, or discoloration are visible. VABYSMO is a clear to opalescent and colorless to brownish-yellow liquid solution.

Prefilled Syringe Description

Figure A

Note: the dose must be set to the 0.05 mL dose mark.

Use aseptic technique to carry out the following preparation steps:

Open Tray and Remove Syringe Cap

1

Peel the lid off the syringe tray and aseptically remove the prefilled syringe.

2

Hold the syringe by the white collar; snap off the syringe cap (see Figure B).

Do not twist off the cap.

Figure B

Attach Injection Filter Needle

3

Aseptically remove the provided injection filter needle from its packaging.

4

Aseptically and firmly attach the injection filter needle onto the syringe Luer lock (see Figure C).

Figure C

5

Carefully remove the needle cap by pulling it straight off.

Dislodge Air Bubbles

6

Hold the syringe with the injection filter needle pointing up. Check the syringe for air bubbles.

7

If there are any air bubbles, gently tap the syringe with your finger until the bubbles rise to the top (see Figure D).

Figure D

Expel Air and Adjust the Dose

8

Hold the syringe at eye level and slowly push the plunger rod until the lower edge of the rubber stopper's dome is aligned with the 0.05 mL dose mark (see Figure E). This will expel the air and the excess solution and set the dose to 0.05 mL.

Ensure that the injection is given immediately after preparation of the dose.

Figure E

2.6 Preparation for Administration - Vial

Before you start
 | Read all the instructions carefully before using VABYSMO.
 | The VABYSMO kit includes a glass vial and transfer filter needle. The glass vial is for a single dose only. The filter needle is for treatment of a single eye.
 | VABYSMO should be stored refrigerated at temperatures between 2°C to 8°C (36°F to 46°F). Do not freeze. Do not shake.
 | Allow VABYSMO to reach room temperature, 20°C to 25°C (68°F to 77°F) before proceeding with the administration. Keep the vial in the original carton to protect from light.
 | The VABYSMO vial may be kept at room temperature for up to 24 hours.
 | The VABYSMO vial should be inspected visually for particulate matter and discoloration prior to administration. VABYSMO is a clear to opalescent and colorless to brownish-yellow liquid solution. Do not use if particulates, cloudiness, or discoloration are visible. Do not use if the packaging, vial and/or transfer filter needle are expired, damaged, or have been tampered with (see Figure F).
 | Figure F
Use aseptic technique to carry out the preparation of the intravitreal injection.
1 | Gather the following supplies:; - One VABYSMO vial (included) - One sterile 5-micron blunt transfer filter needle 18-gauge × 1½ inch (included) - One sterile 1 mL Luer lock syringe with a 0.05 mL dose mark (not included) Note that a 30-gauge injection needle is recommended to avoid increased injection forces that could be experienced with smaller diameter needles. - One sterile injection needle 30-gauge × ½ inch (not included) - Alcohol swab (not included).
2 | To ensure all liquid settles at the bottom of the vial, place the vial upright on a flat surface (for about 1 minute) after removal from packaging (see Figure G). Gently tap the vial with your finger (see Figure H), as liquid may stick to the top of the vial.
 | Figure G | Figure H
3 | Remove the flip-off cap from the vial (see Figure I) and wipe the vial septum with an alcohol swab (see Figure J).
 | Figure I | Figure J
4 | Aseptically and firmly attach the included 18-gauge × 1½ inch transfer filter needle onto a 1 mL Luer lock syringe (see Figure K).
 | Figure K
5 | Using aseptic technique, push the transfer filter needle into the center of the vial septum (see Figure L), push it all the way in, then tilt the vial slightly so that the needle touches the bottom edge of the vial (see Figure M).
 | Figure L | Figure M
6 | Hold the vial slightly inclined and slowly withdraw all the liquid from the vial (see Figure N). Keep the bevel of the transfer filter needle submerged in the liquid, to avoid introduction of air.
 | Figure N
7 | Ensure that the plunger rod is drawn sufficiently back when emptying the vial, in order to completely empty the transfer filter needle (see Figure N).
8 | Disconnect the transfer filter needle from the syringe and dispose of it in accordance with local regulations.
 | Do not use the transfer filter needle for the intravitreal injection.
9 | Aseptically and firmly attach a 30-gauge × ½ inch injection needle onto the Luer lock syringe (see Figure O).
 | Figure O
10 | Carefully remove the plastic needle shield from the needle by pulling it straight off.
11 | To check for air bubbles, hold the syringe with the needle pointing up. If there are any air bubbles, gently tap the syringe with your finger until the bubbles rise to the top (see Figure P).
 | Figure P
12 | Carefully expel the air from the syringe and needle, and slowly depress the plunger to align the rubber stopper tip to the 0.05 mL dose mark. The syringe is ready for the injection (see Figure Q). Ensure that the injection is given immediately after preparation of the dose.
 | Figure Q

2.7 Injection Procedure

The intravitreal injection procedure must be carried out under aseptic conditions, which includes the use of surgical hand disinfection, sterile gloves, a sterile drape and a sterile eyelid speculum (or equivalent), and the availability of sterile paracentesis equipment (if required). Adequate anesthesia and a broad-spectrum microbicide should be administered prior to the injection.

Inject slowly until the rubber stopper reaches the end of the syringe to deliver the volume of 0.05 mL.

Note for the prefilled syringe: Do not recap or detach the injection filter needle from the syringe.

Any unused drug product or waste material should be disposed of in accordance with local regulations.

Immediately following the intravitreal injection, patients should be monitored for elevation in intraocular pressure. Appropriate monitoring may consist of a check for perfusion of the optic nerve head or tonometry. If required, a sterile paracentesis needle should be available. Following intravitreal injection, patients should be instructed to report any symptoms suggestive of endophthalmitis or retinal detachment (e.g., vision loss, eye pain, redness of the eye, photophobia, blurring of vision) without delay [see Patient Counseling Information (17)].

Each syringe should only be used for the treatment of a single eye. If the contralateral eye requires treatment, a new syringe should be used and the sterile field, syringe, gloves, drapes, eyelid speculum, filter, and injection needles should be changed before VABYSMO is administered to the other eye.

3 DOSAGE FORMS AND STRENGTHS

VABYSMO is a clear to opalescent, colorless to brownish-yellow solution available as:

- Injection: 6 mg (0.05 mL of 120 mg/mL solution) in a single-dose prefilled glass syringe
- Injection: 6 mg (0.05 mL of 120 mg/mL solution) in a single-dose glass vial

4 CONTRAINDICATIONS

4.1 Ocular or Periocular Infections

VABYSMO is contraindicated in patients with ocular or periocular infections.

4.2 Active Intraocular Inflammation

VABYSMO is contraindicated in patients with active intraocular inflammation.

4.3 Hypersensitivity

VABYSMO is contraindicated in patients with known hypersensitivity to faricimab or any of the excipients in VABYSMO. Hypersensitivity reactions may manifest as rash, pruritus, urticaria, erythema, or severe intraocular inflammation.

5 WARNINGS AND PRECAUTIONS

5.1 Endophthalmitis and Retinal Detachments

Intravitreal injections, including Vabysmo, have been associated with endophthalmitis and retinal detachments [see Adverse Reactions (6.1)]. Proper aseptic injection techniques must always be used when administering VABYSMO. Patients should be instructed to report any signs or symptoms suggestive of endophthalmitis or retinal detachment without delay, to permit prompt and appropriate management [see Dosage and Administration (2.6) and Patient Counseling Information (17)].

5.2 Increase in Intraocular Pressure

Transient increases in intraocular pressure (IOP) have been seen within 60 minutes of intravitreal injection, including with VABYSMO [see Adverse Reactions (6.1)]. IOP and the perfusion of the optic nerve head should be monitored and managed appropriately [see Dosage and Administration (2.6)].

5.3 Thromboembolic Events

Although there was a low rate of arterial thromboembolic events (ATEs) observed in the VABYSMO clinical trials, there is a potential risk of ATEs following intravitreal use of VEGF inhibitors. ATEs are defined as nonfatal stroke, nonfatal myocardial infarction, or vascular death (including deaths of unknown cause).

The incidence of reported ATEs in the nAMD studies during the first year was 1% (7 out of 664) in patients treated with VABYSMO compared with 1% (6 out of 662) in patients treated with aflibercept [see Clinical Studies (14.1)].

The incidence of reported ATEs in the DME studies from baseline to week 100 was 5% (64 out of 1,262) in patients treated with VABYSMO compared with 5% (32 out of 625) in patients treated with aflibercept [see Clinical Studies (14.2)].

The incidence of reported ATEs in the RVO studies during the first 6 months was 1.1% (7 out of 641) in patients treated with VABYSMO compared with 1.4% (9 out of 635) in patients treated with aflibercept [see Clinical Studies (14.3)].

5.4 Retinal Vasculitis and/or Retinal Vascular Occlusion

Retinal vasculitis and/or retinal vascular occlusion, typically in the presence of intraocular inflammation, have been reported with the use of VABYSMO [see Adverse Reactions (6.2)]. Discontinue treatment with VABYSMO in patients who develop these events. Patients should be instructed to report any change in vision without delay.

6 ADVERSE REACTIONS

The following potentially serious adverse reactions are described elsewhere in the labeling:

- Hypersensitivity [see Contraindications (4)]
- Endophthalmitis and retinal detachments [see Warnings and Precautions (5.1)]
- Increase in intraocular pressure [see Warnings and Precautions (5.2)]
- Thromboembolic events [see Warnings and Precautions (5.3)]
- Retinal Vasculitis and/or Retinal Vascular Occlusion [see Warnings and Precautions (5.4)]

6.1 Clinical Trials Experience

Because clinical trials are conducted under widely varying conditions, adverse reaction rates observed in the clinical trials of a drug cannot be directly compared to rates in other clinical trials of the same or another drug and may not reflect the rates observed in practice.

The data described below reflect exposure to VABYSMO in 2,567 patients, which constituted the safety population in six Phase 3 studies [see Clinical Studies (14.1, 14.2, 14.3)].

Table 1: Common Adverse Reactions (≥ 1%)
Adverse Reactions | VABYSMO |  |  | Active Control (aflibercept)
Adverse Reactions | AMD N=664 | DME N=1,262 | RVO N=641 | AMD N=662 | DME N=625 | RVO N=635
Cataract | 3% | 15% | < 1% | 2% | 12% | 1%
Conjunctival hemorrhage | 7% | 8% | 3% | 8% | 7% | 4%
Vitreous detachment | 3% | 5% | 2% | 3% | 4% | 2%
Vitreous floaters | 3% | 4% | 2% | 2% | 3% | 2%
Retinal pigment epithelial tear [AMD only] | 3% |  |  | 1%
Intraocular pressure increased | 3% | 4% | 1% | 2% | 3% | 3%
Eye pain | 3% | 3% | < 1% | 3% | 3% | < 1%
Intraocular inflammation [Including iridocyclitis, iritis, uveitis, vitritis] | 2% | 1% | 1% | 1% | 1% | < 1%
Eye irritation | 1% | < 1% | < 1% | < 1% | 1% | < 1%
Lacrimation increased | 1% | 1% | 0 | 1% | < 1% | < 1%
Ocular discomfort | 1% | 1% | < 1% | < 1% | < 1% | < 1%

Less common adverse reactions reported in < 1% of the patients treated with VABYSMO were corneal abrasion, eye pruritus, ocular hyperemia, blurred vision, sensation of foreign body, endophthalmitis, conjunctival hyperaemia, visual acuity reduced, visual acuity reduced transiently, vitreous hemorrhage, retinal tear and rhegmatogenous retinal detachment.

6.2 Postmarketing Experience

The following adverse reactions have been identified during postapproval use of VABYSMO. Because these reactions are reported voluntarily from a population of uncertain size, it is not always possible to reliably estimate their frequency or establish a causal relationship to drug exposure.

Eye disorders: retinal vasculitis with or without retinal vascular occlusion.

8 USE IN SPECIFIC POPULATIONS

8.1 Pregnancy

Risk Summary

There are no adequate and well-controlled studies of VABYSMO administration in pregnant women.

Administration of VABYSMO to pregnant monkeys throughout the period of organogenesis resulted in an increased incidence of abortions at intravenous (IV) doses 158 times the human exposure (based on Cmax) of the maximum recommended human dose [see Animal Data]. Based on the mechanism of action of VEGF and Ang-2 inhibitors, there is a potential risk to female reproductive capacity, and to embryo-fetal development. VABYSMO should not be used during pregnancy unless the potential benefit to the patient outweighs the potential risk to the fetus.

All pregnancies have a background risk of birth defect, loss, and other adverse outcomes. The background risk of major birth defects and miscarriage for the indicated population is unknown. In the U.S. general population, the estimated background risk of major birth defects is 2%-4% and of miscarriage is 15%-20% of clinically recognized pregnancies.

Data

Animal Data

An embryo fetal developmental toxicity study was performed on pregnant cynomolgus monkeys. Pregnant animals received 5 weekly IV injections of VABYSMO starting on day 20 of gestation at 1 or 3 mg/kg. A non-dose dependent increase in pregnancy loss (abortions) was observed at both doses evaluated. Serum exposure (Cmax) in pregnant monkeys at the low dose of 1 mg/kg was 158 times the human exposure at the maximum recommended intravitreal dose of 6 mg once every 4 weeks. A no observed adverse effect level (NOAEL) was not identified in this study.

8.2 Lactation

Risk Summary

There is no information regarding the presence of faricimab in human milk, the effects of the drug on the breastfed infant, or the effects of the drug on milk production. Many drugs are transferred in human milk with the potential for absorption and adverse reactions in the breastfed child.

The developmental and health benefits of breastfeeding should be considered along with the mother's clinical need for VABYSMO and any potential adverse effects on the breastfed child from VABYSMO.

8.3 Females and Males of Reproductive Potential

Contraception

Females of reproductive potential are advised to use effective contraception prior to the initial dose, during treatment and for at least 3 months following the last dose of VABYSMO.

Infertility

No studies on the effects of faricimab on human fertility have been conducted and it is not known whether faricimab can affect reproduction capacity. Based on the mechanism of action, treatment with VABYSMO may pose a risk to reproductive capacity.

8.4 Pediatric Use

The safety and efficacy of VABYSMO in pediatric patients have not been established.

8.5 Geriatric Use

In the six clinical studies, approximately 58% (1,496/2,571) of patients randomized to treatment with VABYSMO were ≥ 65 years of age. No significant differences in efficacy or safety of faricimab were seen with increasing age in these studies. No dose adjustment is required in patients 65 years and above.

11 DESCRIPTION

Faricimab-svoa is a humanized bispecific immunoglobulin G1 (IgG1) antibody that binds both vascular endothelial growth factor A (VEGF-A) and angiopoietin-2 (Ang-2). The fragment crystallizable (Fc) region of faricimab was engineered by selected point mutations to abolish binding interactions with Fcγ and FcRn receptors. Faricimab-svoa has a total molecular weight of approximately 149 kDa and is produced by recombinant DNA technology using mammalian Chinese Hamster Ovary (CHO) cell culture.

VABYSMO (faricimab-svoa) injection is a sterile, clear to opalescent, colorless to brownish-yellow solution in a single-dose prefilled glass syringe or glass vial for intravitreal administration. Each single-dose prefilled syringe or single-dose vial is designed to deliver 0.05 mL (50 microliters) of solution containing 6 mg faricimab-svoa, L-histidine (155 mcg), L-methionine (52.2 mcg), polysorbate 20 (20 mcg), sodium chloride (73.1 mcg), D-sucrose (2.74 mg) and Water for Injection, adjusted to pH 5.5 with acetic acid. The product does not contain an anti-microbial preservative.

12 CLINICAL PHARMACOLOGY

12.1 Mechanism of Action

Faricimab is a humanized bispecific antibody that acts through inhibition of two pathways by binding to VEGF-A and Ang-2. By inhibiting VEGF-A, faricimab suppresses endothelial cell proliferation, neovascularization and vascular permeability. By inhibiting Ang-2, faricimab is thought to promote vascular stability and desensitize blood vessels to the effects of VEGF-A. Ang-2 levels are increased in some patients with nAMD, DME, and RVO. The contribution of Ang-2 inhibition to the treatment effect and clinical response for nAMD, DME, and RVO has yet to be established.

12.2 Pharmacodynamics

Increased retinal thickness, assessed by optical coherence tomography (OCT), is associated with nAMD, DME and macular edema following RVO. Leakage of blood and fluid from choroidal neovascularization, assessed by fluorescein angiography, is associated with nAMD. Reductions in CST were observed across all treatment arms throughout the six Phase 3 studies in nAMD, DME, and RVO.

12.3 Pharmacokinetics

Absorption/Distribution

Maximum faricimab plasma concentrations (Cmax) are estimated to occur approximately 2 days post-dose. Mean (±SD) free faricimab (unbound to VEGF-A and Ang-2) plasma Cmax are estimated to be 0.23 (0.07) mcg/mL and 0.22 (0.07) mcg/mL in nAMD and in DME patients, respectively. After repeated intravitreal administrations, mean plasma free faricimab trough concentrations are predicted to be 0.002-0.003 mcg/mL for every 8 weeks (Q8W) dosing and 0.021-0.029 mcg/mL for every 4 weeks (Q4W) dosing. Although not directly measured in the vitreous, no accumulation of faricimab is expected in the vitreous and no accumulation has been observed in plasma when faricimab has been administered as repeat doses in the vitreous.

Metabolism/Elimination

Metabolism and elimination of faricimab has not been fully characterized. Faricimab is expected to be catabolized in lysosomes to small peptides and amino acids, which may be excreted renally, in a similar manner to the elimination of endogenous IgG. The estimated mean apparent systemic half-life of faricimab is approximately 7.5 days.

Specific Populations

The systemic pharmacokinetics of faricimab were not influenced by gender, race, or mild to severe renal impairment (i.e., estimated normalized creatinine clearance by Cockroft-Gault equation: 15 to 89 mL/min/1.73 m^2). The effect of severe renal impairment or any degree of hepatic impairment on the pharmacokinetics of VABYSMO is unknown. No special dosage modification is required for any of the populations that have been studied (e.g., elderly, gender, race).

Population pharmacokinetic analysis indicated that the pharmacokinetics of faricimab are comparable in nAMD, DME, and RVO patients.

12.6 Immunogenicity

The immunogenicity of VABYSMO was evaluated in plasma samples. The immunogenicity data reflect the percentage of patients whose test results were considered positive for antibodies to VABYSMO in immunoassays. The detection of an immune response is highly dependent on the sensitivity and specificity of the assays used, sample handling, timing of sample collection, concomitant medications, and underlying disease. For these reasons, comparison of the incidence of antibodies to VABYSMO with the incidence of antibodies to other products may be misleading.

There is a potential for an immune response in patients treated with VABYSMO. In the nAMD, DME, and RVO studies, the pre-treatment incidence of anti-faricimab antibodies was approximately 0.8 to 1.8%. After initiation of dosing, the incidence of anti-faricimab antibodies was approximately 8% to 10.4% in patients treated with VABYSMO across studies. As with all therapeutic proteins, there is a potential for immunogenicity with VABYSMO.

13 NONCLINICAL TOXICOLOGY

13.1 Carcinogenesis, Mutagenesis, Impairment of Fertility

No carcinogenicity or mutagenicity data are available for VABYSMO injection in animals or humans.

Based on the anti-VEGF and Ang-2 mechanisms of action, treatment with VABYSMO may pose a risk to reproductive capacity [see Females and Males of Reproductive Potential (8.3)].

14 CLINICAL STUDIES

14.1 Neovascular (wet) Age-Related Macular Degeneration (nAMD)

The safety and efficacy of VABYSMO were assessed in two randomized, multi-center, double-masked, active comparator-controlled, 2-year studies (TENAYA – NCT03823287 and LUCERNE – NCT03823300) in patients with nAMD.

A total of 1,329 newly diagnosed, treatment-naïve patients were enrolled in these studies, and 664 patients received at least one dose of VABYSMO. Patient ages ranged from 50 to 99 with a mean of 75.9 years. The studies were identically designed two year studies. Patients were randomized in a 1:1 ratio to one of two treatment arms: 1) aflibercept 2 mg administered fixed every 8 weeks (Q8W) after three initial monthly doses; and VABYSMO 6 mg (0.05 mL of 120 mg/mL solution) administered by intravitreal injection every 4 weeks (approximately every 28 ± 7 days, monthly) for the first 4 doses, followed by optical coherence tomography and visual acuity evaluations 8 and 12 weeks later to determine whether to give a 6 mg (0.05 mL of 120 mg/mL solution) dose via intravitreal injection on one of the following three regimens: 1) Weeks 28 and 44; (also referred to as Q16W dosing); 2) Weeks 24, 36 and 48 (also referred to as Q12W dosing); or 3) Weeks 20, 28, 36 and 44 (also referred to as Q8W dosing). However, the utility of these criteria to guide dosing intervals has not been established.

At week 48, after 4 initial monthly doses in the VABYSMO arm, 45% of patients received the Weeks 28 and 44 dosing, 33% of patients received the Weeks 24, 36 and 48 dosing, and the remaining 22% of patients received dosing every 8 weeks. These percentages are reflective of what happened within the conduct of these trials and indicate that some patients did well on two (2) doses spaced 16 weeks apart, or three (3) doses spaced 12 weeks apart, but the percentages may not be generalizable to a broader nAMD population for a variety of reasons. The inclusion/exclusion criteria limited enrollment to a select subset of treatment-naïve, newly diagnosed nAMD patients and there is no empirical data that a similar magnitude would be observed if eligibility criteria allowed for broader enrollment. The disease activity criteria, which was instrumental in determining dose frequency, is unvalidated. Stricter criteria would have changed how patients were treated resulting in different percentages of subjects in each dose interval cohort. There was not a similarly dosed aflibercept arm for comparison, which makes the percentages difficult to interpret.

Both studies demonstrated non-inferiority to the comparator control (aflibercept) at the primary endpoint, defined as the mean change from baseline in Best Corrected Visual Acuity (BCVA) when averaged over the week 40, 44, and 48 visits and measured by the Early Treatment Diabetic Retinopathy Study (ETDRS) letter chart. The primary endpoint analysis was a non- inferiority comparison for the mean change in BCVA between the aflibercept and the VABYSMO arm. The lower bound of the 95% confidence interval for the mean change in BCVA could not be lower than minus 4 letters to declare non-inferiority. In both studies, VABYSMO treated patients had a non-inferior mean change from baseline in BCVA compared to patients treated with aflibercept. Detailed results of both studies are shown in Table 2, Figure 1, and Figure 2 below. The clinical efficacy for the second year of the study has not been reviewed.

Table 2: Primary Endpoint Results [Average of weeks 40, 44 and 48] in the TENAYA and LUCERNE Studies
 | TENAYA |  | LUCERNE
 | VABYSMO N = 334 | Aflibercept N = 337 | VABYSMO N = 331 | Aflibercept N = 327
Mean change in BCVA as measured by ETDRS letter score from baseline (95% CI) | 5.8 (4.6, 7.1) | 5.1 (3.9, 6.4) | 6.6 (5.3, 7.8) | 6.6 (5.3, 7.8)
Difference in LS mean (95% CI) | 0.7 (-1.1, 2.5) |  | 0.0 (-1.7, 1.8)
BCVA: Best Corrected Visual Acuity
ETDRS: Early Treatment Diabetic Retinopathy Study
CI: Confidence Interval
LS: Least Square

Figure 1: Mean Change in Visual Acuity from Baseline to Week 48 in TENAYA

Figure 2: Mean Change in Visual Acuity from Baseline to Week 48 in LUCERNE

Treatment effects in evaluable subgroups (e.g., age, gender, race, baseline visual acuity) in each study were consistent with the results in the overall population.

14.2 Diabetic Macular Edema (DME)

The safety and efficacy of VABYSMO were assessed in two randomized, multi-center, double-masked, active comparator-controlled 2-year studies (YOSEMITE – NCT03622580 and RHINE – NCT03622593) in patients with DME.

A total of 1,891 diabetic patients were enrolled in the two studies with a total of 1,262 patients treated with at least one dose of VABYSMO. Patient ages ranged from 24 to 91 with a mean of 62.2 years. The overall population included both anti-VEGF naïve patients (78%) and patients who had been previously treated with a VEGF inhibitor prior to study participation (22%).

The studies were identically designed two year studies. Patients were randomized in a 1:1:1 ratio to one of three treatment regimens: 1) aflibercept Q8W, patients received fixed aflibercept 2 mg administered every 8 weeks (Q8W) after the first five monthly doses; 2) VABYSMO Q8W, patients received fixed VABYSMO 6 mg administered Q8W after the first six monthly doses; and 3) VABYSMO Variable, patients received VABYSMO 6 mg administered every 4 weeks for at least 4 doses and until the central subfield thickness (CST) of the macula measured by optical coherence tomography was less than approximately 325 microns, then the interval of dosing was modified by up to 4 week interval extensions or reductions of up to 8 week interval increments based on CST and visual acuity disease activity criteria at study drug dosing visits.

After 4 initial monthly doses, the patients in the VABYSMO Variable arm received between a minimum of 1 and a maximum of 21 total injections (median of 7 injections) through Week 96 inclusive. At Week 56, 32% of patients had completed at least one Q12W interval followed by one full Q16W interval. Seventeen percent (17%) of patients were treated on Q8W and/or Q4W dosing intervals through Week 56 (7% only on Q4W). These percentages are reflective of what happened within the conduct of these trials, but the percentages may not be generalizable to a broader DME population.

The inclusion/exclusion criteria limited enrollment to a select subset of DME patients and there is no empirical data that a similar magnitude would be observed if eligibility criteria allowed for broader enrollment. The disease activity criteria, which were instrumental in determining dose frequency, are unvalidated. Different criteria would have changed how patients were treated resulting in different percentages of subjects in each dose interval cohort. There was not a similarly dosed aflibercept arm for comparison which makes the percentages difficult to interpret.

Both studies demonstrated non-inferiority to the comparator control (aflibercept) at the primary endpoint, defined as the mean change from baseline in BCVA at year 1 (average of the Week 48, 52, and 56 visits), measured by the ETDRS Letter Score. The primary endpoint analysis was a non-inferiority comparison for the mean change in BCVA between the aflibercept and VABYSMO arms. The lower bound of the 97.5% confidence interval for the mean change in BCVA could not be lower than minus 4 letters to declare non-inferiority. In both studies, VABYSMO Q8W and VABYSMO Variable treated patients had a non-inferior mean change from baseline in BCVA to the patients treated with aflibercept Q8W at the year 1 primary endpoint. Detailed results of both studies are shown in Table 3, Figure 3, and Figure 4 below.

Table 3: Efficacy Results at Year 1 [Average of Weeks 48, 52, 56] and at Year 2 [Average of Weeks 92, 96, 100] in the YOSEMITE and RHINE Studies
 | YOSEMITE |  |  |  |  |  | RHINE
 | Year 1 |  |  | Year 2 |  |  | Year 1 |  |  | Year 2
 | VABYSMO Q8W N = 315 | VABYSMO Variable N = 313 | Aflibercept Q8W N = 312 | VABYSMO Q8W N = 262 | VABYSMO Variable N = 270 | Aflibercept Q8W N = 259 | VABYSMO Q8W N = 317 | VABYSMO Variable N = 319 | Aflibercept Q8W N = 315 | VABYSMO Q8W N = 259 | VABYSMO Variable N = 282 | Aflibercept Q8W N = 254
Mean change in BCVA as measured by ETDRS letter score from baseline (97.5% CI year 1 and 95% CI year 2) | 10.7 (9.4, 12.0) | 11.6 (10.3, 12.9) | 10.9 (9.6, 12.2) | 10.7 (9.4, 12.1) | 10.7 (9.4, 12.1) | 11.4 (10.0, 12.7) | 11.8 (10.6, 13.0) | 10.8 (9.6, 11.9) | 10.3 (9.1, 11.4) | 10.9 (9.5, 12.3) | 10.1 (8.7, 11.5) | 9.4 (7.9, 10.8)
Difference in LS mean (97.5% CI year 1 and 95% CI year 2) | -0.2 (-2.0, 1.6) | 0.7 (-1.1, 2.5) |  | -0.7 [A non-inferiority margin was not available for year 2] | -0.7 |  | 1.5 (-0.1, 3.2) | 0.5 (-1.1, 2.1) |  | 1.5 | 0.7
BCVA: Best Corrected Visual Acuity
ETDRS: Early Treatment Diabetic Retinopathy Study
CI: Confidence Interval
LS: Least Square

Figure 3: Mean Change in Visual Acuity from Baseline to Year 2 (Week 100) in YOSEMITE

Figure 4: Mean Change in Visual Acuity from Baseline to Year 2 (Week 100) in RHINE

Treatment effects in the subgroup of patients who were anti-VEGF naïve prior to study participation were similar to those observed in the overall population. Treatment effects in evaluable subgroups (e.g., by age, gender, race, baseline HbA1c, baseline visual acuity) in each study were generally consistent with the results in the overall population.

14.3 Macular Edema Following Retinal Vein Occlusion (RVO)

The safety and efficacy of VABYSMO were assessed in two randomized, multicenter, double-masked, studies (BALATON – NCT04740905 in patients with macular edema following branch retinal vein occlusion, and COMINO – NCT04740931 in patients with macular edema following central retinal vein occlusion/hemiretinal vein occlusion). Active comparator-controlled data are available through month 6.

A total of 1,282 newly diagnosed, treatment-naïve patients were enrolled in these studies, of which 641 patients received at least one dose of VABYSMO through 6 months. Patient ages ranged from 28 to 93 with a mean of 64 years, and 22 to 100 with a mean of 65 years in BALATON and COMINO, respectively.

In both studies, patients were randomized in a 1:1 ratio to either 6 mg VABYSMO administered every 4 weeks, or the control arm receiving aflibercept 2 mg injections every 4 weeks for a total of 6 injections.

In both studies, the VABYSMO 6 mg Q4W arm demonstrated non-inferiority to the comparator control (aflibercept) arm for the primary endpoint, which was defined as the change from baseline in BCVA at week 24, measured by the ETDRS Letter Score. The primary endpoint analysis was a non-inferiority comparison for the mean change in BCVA between the aflibercept and VABYSMO arms, where the lower bound of the 95% confidence interval for the mean change in BCVA could not be lower than minus 4 letters to declare non-inferiority.

Detailed results for both BALATON and COMINO studies are shown in Table 4, Figure 5, and Figure 6 below.

Table 4: Primary Endpoint Results at Week 24 in the BALATON and COMINO Studies
 | BALATON |  | COMINO
 | VABYSMO N = 276 | Aflibercept N = 277 | VABYSMO N = 366 | Aflibercept N = 363
Mean change in BCVA as measured by ETDRS letter score from baseline (95% CI) | 16.9 (15.7, 18.1) | 17.5 (16.3, 18.6) | 16.9 (15.4, 18.3) | 17.3 (15.9, 18.8)
Difference in LS mean (95% CI) | -0.6 (-2.2, 1.1) |  | -0.4 (-2.5, 1.6)
BCVA: Best Corrected Visual Acuity
ETDRS: Early Treatment Diabetic Retinopathy Study
CI: Confidence Interval
LS: Least Square

Figure 5: Mean Change in Visual Acuity from Baseline to Week 24 in BALATON

Figure 6: Mean Change in Visual Acuity from Baseline to Week 24 in COMINO

16 HOW SUPPLIED/STORAGE AND HANDLING

16.1 How Supplied

VABYSMO (faricimab-svoa) injection is supplied as a clear to opalescent, colorless to brownish-yellow solution as 6 mg (0.05 mL of 120 mg/mL solution) in a single-dose prefilled syringe or single-dose vial. Each prefilled syringe or vial is for treatment of a single eye.

VABYSMO is supplied in the following presentations:

NDC NUMBER | CARTON TYPE | CARTON CONTENTS
50242-096-06 | Prefilled Syringe | one 6 mg (0.05 mL of 120 mg/mL solution) single-dose prefilled glass syringe, in a sealed tray one sterile injection filter needle (30-gauge × ½ inch, 0.30 mm × 12.7 mm, Extra Thin Wall) one Prescribing Information
50242-096-01 | Vial | one 6 mg (0.05 mL of 120 mg/mL solution) single-dose glass vial one sterile 5-micron blunt transfer filter needle (18-gauge × 1½ inch, 1.2 mm × 40 mm) one Prescribing Information

16.2 Storage and Handling

Store VABYSMO in the refrigerator between 2°C to 8°C (36°F to 46°F). Do not freeze. Do not shake. Keep the sealed tray containing the prefilled syringe or the vial in the original carton to protect from light.

Prior to use, the unopened prefilled syringe or glass vial of VABYSMO may be kept at room temperature, 20°C to 25°C (68°F to 77°F), for up to 24 hours. Ensure that the injection is given immediately after preparation of the dose.

17 PATIENT COUNSELING INFORMATION

Advise patients that in the days following VABYSMO administration, patients are at risk of developing endophthalmitis, retinal detachment, intraocular inflammation and retinal vasculitis with or without retinal vascular occlusion. If the eye becomes red, sensitive to light, painful, or develops a change in vision, advise the patient to seek immediate care from an ophthalmologist [see Warnings and Precautions (5)].

Patients may experience temporary visual disturbances after an intravitreal injection with VABYSMO and the associated eye examinations [see Adverse Reactions (6)]. Advise patients not to drive or use machinery until visual function has recovered sufficiently.

VABYSMO® [faricimab-svoa]
Manufactured by:
Genentech, Inc.
A Member of the Roche Group
1 DNA Way
South San Francisco, CA 94080-4990
U.S. License No.: 1048

VABYSMO is a trademark of Genentech, Inc.
©2024 Genentech, Inc.

PRINCIPAL DISPLAY PANEL - 6 mg Vial Carton

Vabysmo®
(faricimab-svoa)
Injection

NDC 50242-096-01

6 mg (0.05 mL of 120 mg/mL solution)

For Intravitreal Injection. Single-Dose Vial.
Discard Unused Portion.

1 single-dose vial
1 transfer filter needle

Rx only
Genentech

11028025

PRINCIPAL DISPLAY PANEL - 6 mg Syringe Carton

Vabysmo®
(faricimab-svoa)
Injection

NDC 50242-096-06

6 mg (0.05 mL of 120 mg/mL solution)

For Intravitreal Injection
Single-Dose Prefilled Syringe

ATTENTION:
Only use the provided injection filter needle for the administration.
The dose must be set to the 0.05 mL dose mark (see enclosed prescribing information).

1 Sterile Prefilled Syringe
1 Sterile Injection Filter Needle

Rx only
Genentech

11005157